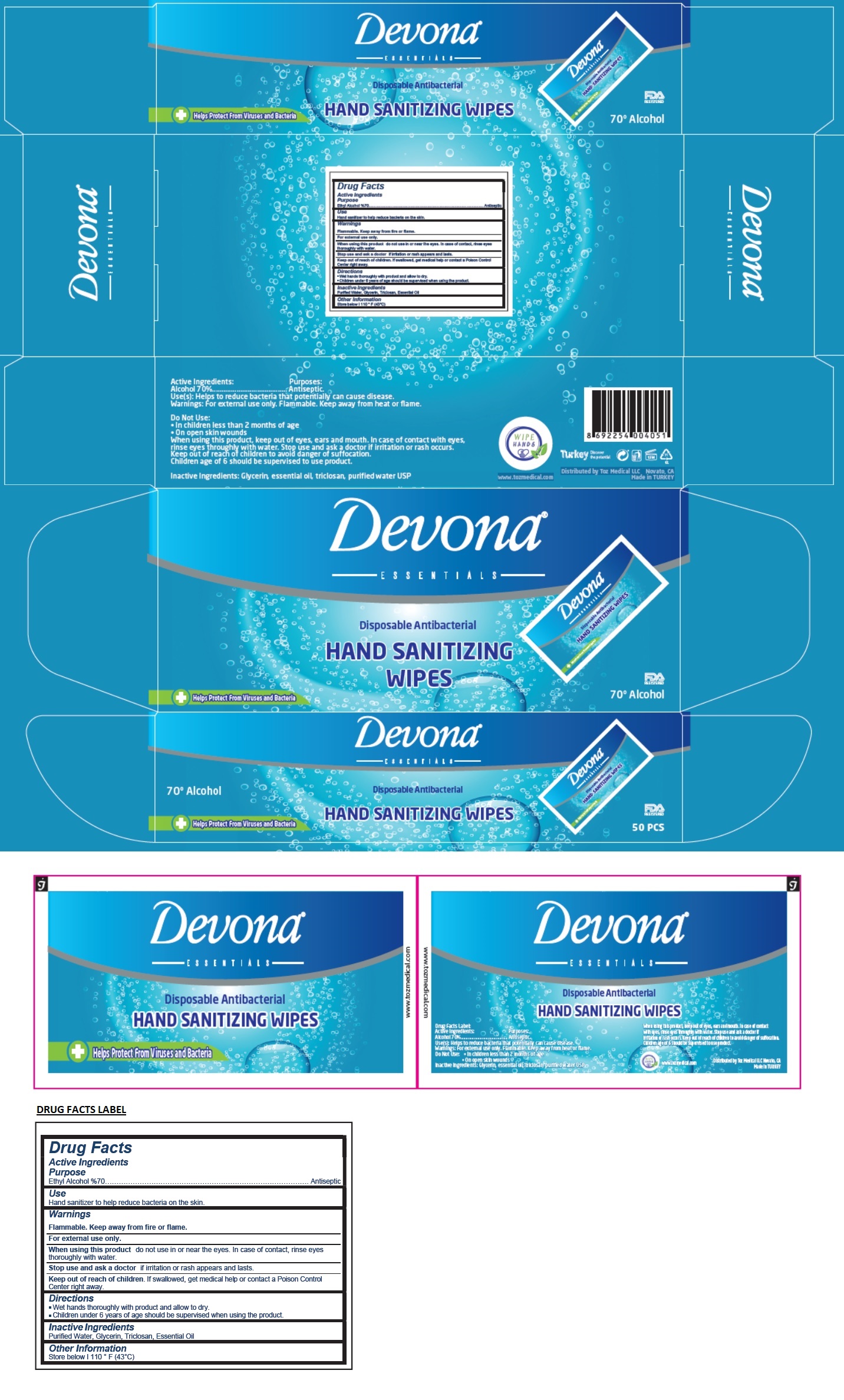 DRUG LABEL: Devona HAND SANITIZING WIPES
NDC: 78576-415 | Form: CLOTH
Manufacturer: GULBAHCE KOZM KIMYA TEM URUNLERI KONF AMB SAN VE TIC LTD STI-BURSA NILUFER SUBESI
Category: otc | Type: HUMAN OTC DRUG LABEL
Date: 20200604

ACTIVE INGREDIENTS: ALCOHOL 70 mL/100 mL
INACTIVE INGREDIENTS: WATER; GLYCERIN; TRICLOSAN

Devona® ESSENTIALS Disposable Antibacterial HAND SANITIZING WIPES

Active Ingredients

Ethyl Alcohol %70

Purpose

Antiseptic

Use

Hand sanitizer to help reduce bacteria on the skin.

Warnings

Flammable. Keep away from fire or flame.

For external use only

When using this product do not use in or near the eyes. In case of contact, rinse eyes thoroughly with water.
Stop use and ask a doctor if irritation or rash appears and lasts.

Keep out of reach of children. If swallowed, get medical help or contact a Poison Control Center right away.

Directions

■ Wet hands thoroughly with product and allow to dry.
■ Children under 6 years of age should be supervised when using the product.

Inactive Ingredients

Purified Water, Glycerin, Triclosan, Essential Oil

Other Information

Store below | 110 ° F (43°C)

+ Helps Protect From Viruses and Bacteria

FDA REGISTERED

WIPE HANDS

Turkey Discover the potential

www.tozmedical.com

Distributed by Toz Medical LLC Novato, CA
Made in TURKEY